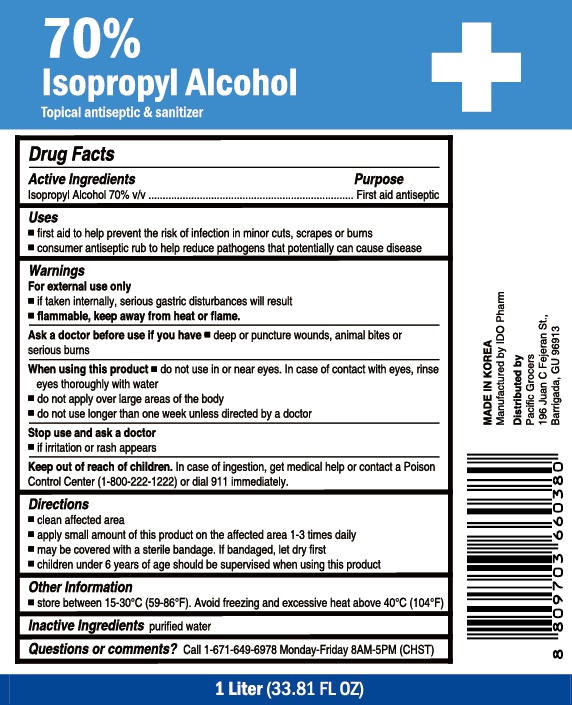 DRUG LABEL: 70% Isopropyl Alcohol
NDC: 77039-010 | Form: LIQUID
Manufacturer: IDO PHARM
Category: otc | Type: HUMAN OTC DRUG LABEL
Date: 20250130

ACTIVE INGREDIENTS: ISOPROPYL ALCOHOL 70 g/100 mL
INACTIVE INGREDIENTS: WATER

IDO PHARM - 70% Isopropyl Alcohol (Topical antiseptic & sanitizer)

ACTIVE INGREDIENT

Isopropyl Alcohol 70% v/v

INACTIVE INGREDIENT

Water

PURPOSE

First aid to help prevent the risk of infection in minor cuts, scrapes or burns.

Keep out of reach of children

INDICATIONS AND USAGE

For the external use only

WARNINGS

For external use only

- If taken internally, serious gastric disturbances will result
- flammable, keep away from heat or flame

Ask a doctor before use if you have deep or puncture wounds, animal bites or serious burns

When using this product

- do not use in or near eyes. In case of contact with eyes, rinse eyes thoroughly with water
- do not apply over large areas of the body
- do not use longer than one week unless directed by a doctor

Stop use and ask a doctor if irritation or rash appears

Keep out of reach of children. In case of ingestion, get medical help or contact a Poison Control Center 1-800-222-1222 or dial 911 immediately

DOSAGE AND ADMINISTRATION

Clean affected area

Apply small amount of this product on the affected area 1-3 times daily

May be covered with a sterile bandage. If bandaged, let dry first

children under 6 years of age should be supervised when using this product